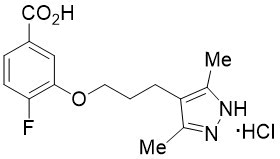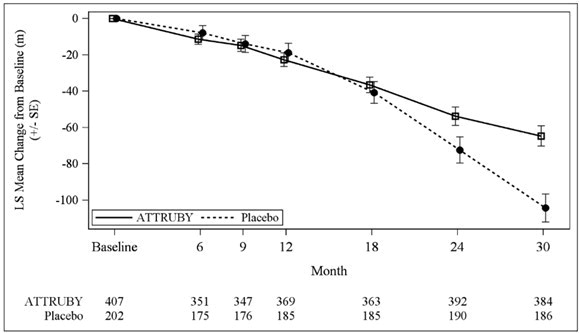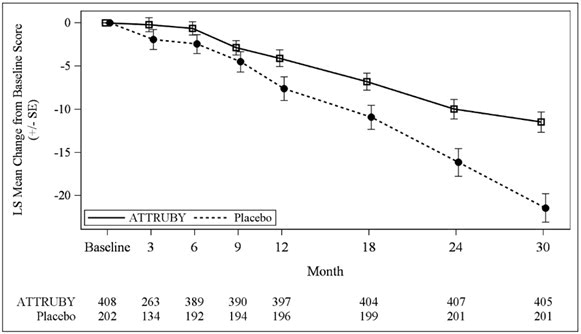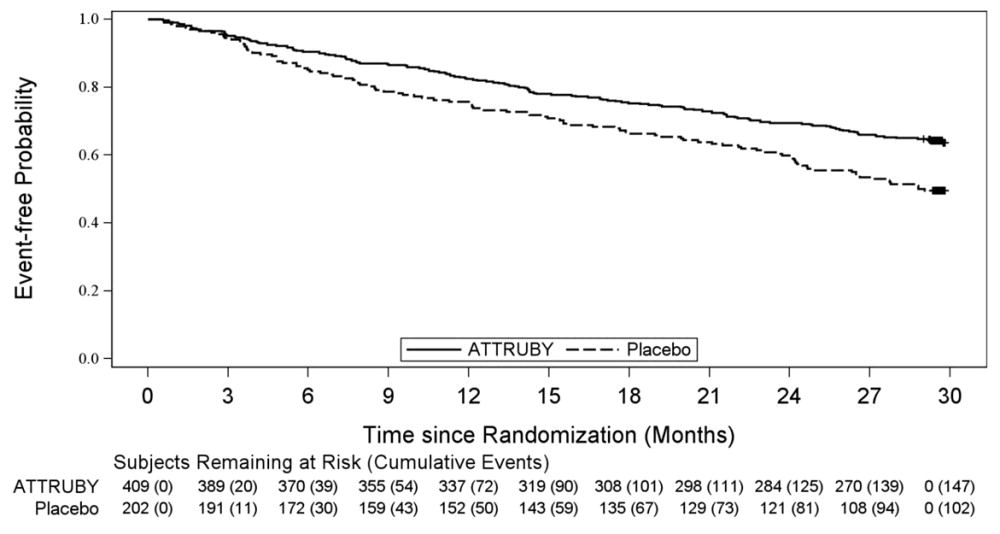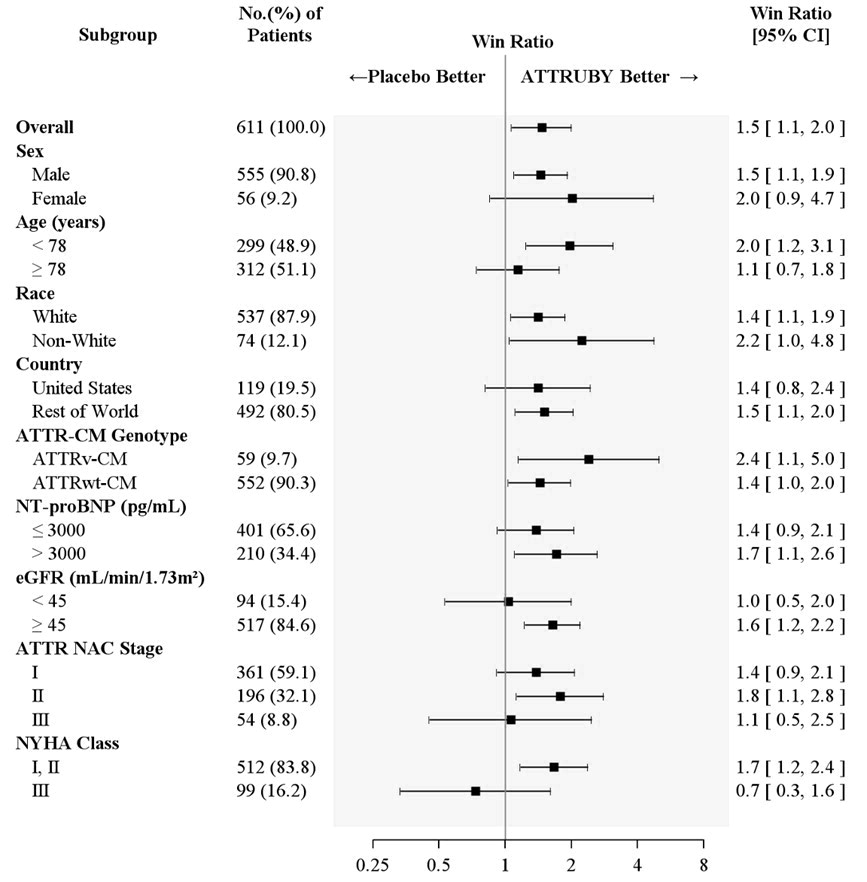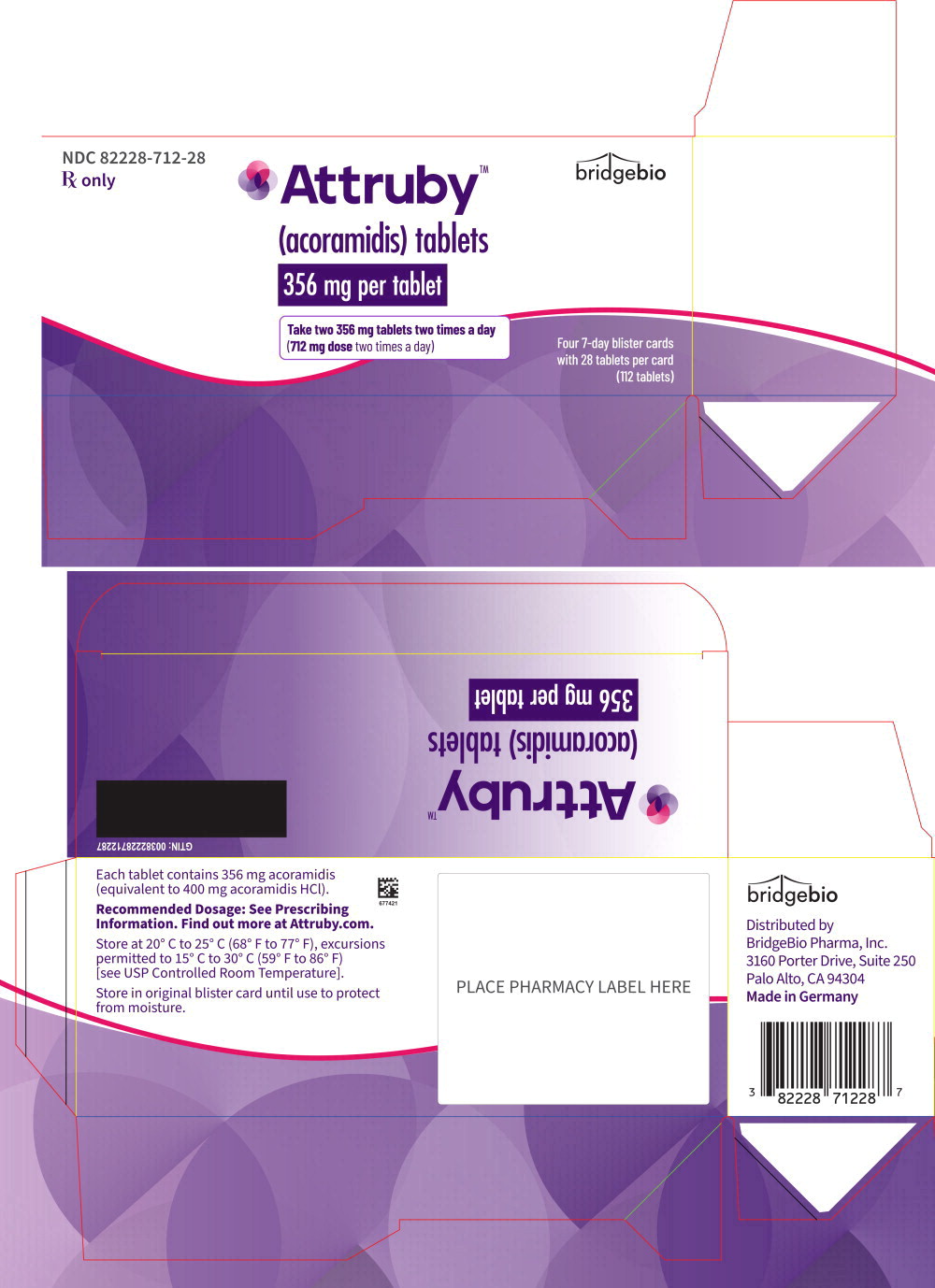 DRUG LABEL: Attruby
NDC: 82228-712 | Form: TABLET, FILM COATED
Manufacturer: BridgeBio Pharma, Inc.
Category: prescription | Type: HUMAN PRESCRIPTION DRUG LABEL
Date: 20251216

ACTIVE INGREDIENTS: acoramidis hydrochloride 356 mg/1 1
INACTIVE INGREDIENTS: Microcrystalline Cellulose; Croscarmellose Sodium; Silicon Dioxide; Magnesium Stearate; POLYVINYL ALCOHOL GRAFT POLYETHYLENE GLYCOL COPOLYMER (3:1; 45000 MW); Talc; Titanium Dioxide; Glyceryl Mono- And Dicaprylocaprate; Polyvinyl Alcohol, Unspecified; Ferrosoferric Oxide; Propylene Glycol; Hypromellose 2910 (6 MPA.S)

HIGHLIGHTS OF PRESCRIBING INFORMATION

These highlights do not include all the information needed to use ATTRUBY safely and effectively. See full prescribing information for ATTRUBY.
ATTRUBY™ (acoramidis) tablets, for oral administration,
Initial U.S. Approval: 2024

1 INDICATIONS AND USAGE

ATTRUBY is a transthyretin stabilizer indicated for the treatment of the cardiomyopathy of wild-type or variant transthyretin-mediated amyloidosis (ATTR-CM) in adults to reduce cardiovascular death and cardiovascular-related hospitalization. (1, 2.1)

2 DOSAGE AND ADMINISTRATION

The recommended dosage of ATTRUBY is 712 mg orally twice daily. (2.1)

3 DOSAGE FORMS AND STRENGTHS

Tablets: 356 mg acoramidis (3)

4 CONTRAINDICATIONS

None. (4)

To report SUSPECTED ADVERSE REACTIONS, contact BridgeBio Pharma Inc. at 1-844-550-2246 or FDA at 1-800-FDA-1088 or www.fda.gov/medwatch.

FULL PRESCRIBING INFORMATION

1 INDICATIONS AND USAGE

ATTRUBY is indicated for the treatment of the cardiomyopathy of wild-type or variant transthyretin-mediated amyloidosis (ATTR-CM) in adults to reduce cardiovascular death and cardiovascular-related hospitalization.

2 DOSAGE AND ADMINISTRATION

2.1 Recommended Dosage

The recommended dosage of ATTRUBY is 712 mg orally twice daily (with or without food). Swallow tablets whole; do not cut, crush, or chew.

3 DOSAGE FORMS AND STRENGTHS

ATTRUBY is available as 356 mg acoramidis, white, film-coated, oval tablets, printed with the BridgeBio company logo followed by “ACOR” in black ink on one side.

4 CONTRAINDICATIONS

None.

6 ADVERSE REACTIONS

6.1 Clinical Trials Experience

Because clinical trials are conducted under widely varying conditions, adverse reaction rates observed in the clinical trials of a drug cannot be directly compared to rates in the clinical trials of another drug and may not reflect the rates observed in practice.

The safety data reflect the exposure of 421 participants with ATTR-CM to ATTRUBY 712 mg (administered as two 356 mg tablets) administered orally twice daily in a randomized, double-blind, placebo-controlled trial of 30 months fixed treatment duration. The median duration of exposure to ATTRUBY in the safety population was 29 months. There was a higher frequency of gastrointestinal (GI) adverse reactions such as diarrhea 11.6% versus 7.6% and upper abdominal pain 5.5% versus 1.4% in the ATTRUBY versus placebo group, respectively. The majority of these GI adverse reactions were categorized as mild and resolved without drug discontinuation.

A similar proportion of ATTRUBY-treated and placebo-treated participants discontinued study drug because of an adverse event (9.3% and 8.5%, respectively).

Laboratory Tests

Increase in Serum Creatinine and Decrease in eGFR

Initiation of ATTRUBY causes an increase in serum creatinine and decrease in eGFR which generally occurs within 4 weeks of starting therapy and stabilizes. In a trial of adults with ATTR-CM, a mean increase in serum creatinine of 0.2 and 0.0 mg/dL and a mean decrease in eGFR of 8.2 and 0.7 mL/min/1.73 m^2 was observed in the ATTRUBY and placebo groups, respectively, at Day 28. The changes in serum creatinine and eGFR were reversible after treatment discontinuation.

7 DRUG INTERACTIONS

UDP-glucuronosyltransferases (UGT) Inducers and Strong CYP3A Inducers

Acoramidis is metabolized by UGT enzyme-mediated glucuronidation. Concomitant use of UGT inducers can potentially decrease acoramidis exposure. While acoramidis is not metabolized by CYP3A, strong CYP3A inducers can also induce UGT enzymes. Avoid concomitant use of ATTRUBY with UGT inducers and strong CYP3A inducers.

Sensitive Cytochrome P450 2C9 (CYP2C9) substrates

Acoramidis inhibits CYP2C9 and may result in an increase in CYP2C9 substrate concentrations when these drugs are co administered. Consider more frequent monitoring of patients for evidence of increased exposure (for example, signs of exposure related toxicity) when ATTRUBY is co administered with sensitive CYP2C9 substrates.

8 USE IN SPECIFIC POPULATIONS

8.1 Pregnancy

Risk Summary

Available data with acoramidis use in pregnant women are insufficient to establish a drug associated risk of major birth defects, miscarriage or other adverse maternal or fetal outcomes. In animal reproductive studies in rats and rabbits, no embryofetal abnormalities were observed at exposures up to 34 times and 13 times the clinical exposure at the maximum recommended human dose, respectively (see Data).

The background risk of major birth defects and miscarriage for the indicated population is unknown. All pregnancies have a background risk of birth defects, loss, or other adverse outcomes. In the U.S. general population, the estimated background risk of major birth defects and miscarriage in clinically recognized pregnancies is 2% to 4% and 15% to 20%, respectively.

Report pregnancies to the BridgeBio reporting line at 1-844-550-2246.

Data

Animal Data

In pregnant rats, oral administration of acoramidis (0, 50, 350, and 1,000 mg/kg/day) throughout organogenesis did not result in any adverse effects on embryofetal development at up to 1,000 mg/kg/day, approximately 34 times the clinical exposure at the maximum recommended human dose (MRHD) based on AUC.

In pregnant rabbits, oral administration of acoramidis (0, 25, 75, and 200 mg/kg/day) throughout organogenesis resulted in increased pre-implantation loss at 200 mg/kg/day, a dose that caused maternal toxicity (26% reduced body weight gain). No embryofetal abnormalities were observed at 200 mg/kg/day, approximately 13 times the clinical exposure at the MRHD based on AUC.

In a pre- and postnatal developmental toxicity study, pregnant rats received oral administration of acoramidis at doses of 0, 50, 350, or 1,000 mg/kg/day throughout pregnancy and lactation (Gestation Day 6 to Lactation Day 20). Maternal death, body weight reduction, and decreased number of females with live born pups (due to increase in resorbed litters) were observed at 1,000 mg/kg/day, approximately 43 times the clinical exposure at the MRHD based on AUC. Decreased body weight gain from the neonatal period to weaning and learning deficits were observed in the offspring of dams given 1,000 mg/kg/day. No adverse effects on pre- and postnatal development were observed at 350 mg/kg/day, approximately 18 times the clinical exposure at the MRHD based on AUC.

8.2 Lactation

Risk Summary

There are no available data on the presence of acoramidis in either human or animal milk or the effects of the drug on the breastfed infant or maternal milk production. The developmental and health benefits of breastfeeding should be considered along with the mother's clinical need for ATTRUBY and any potential adverse effects on the breastfed child from ATTRUBY or from the underlying maternal condition.

8.4 Pediatric Use

The safety and effectiveness of ATTRUBY have not been established in pediatric patients.

8.5 Geriatric Use

No dosage adjustment is required for elderly patients (≥65 years) [see Clinical Pharmacology (12.3)]. Of the total number of participants randomized in the clinical study (n=632), 97% were 65 years and over, with a median age of 78 years.

10 OVERDOSAGE

There is no clinical experience with overdose. In case of suspected overdose, treatment should be symptomatic and supportive.

11 DESCRIPTION

ATTRUBY contains 356 mg acoramidis equivalent to 400 mg acoramidis HCl.

Acoramidis HCl is a transthyretin stabilizer. The chemical name of acoramidis HCl is 3-[3-(3,5-dimethyl-1H-pyrazol-4-yl)propoxy]-4-fluorobenzoic acid hydrochloride. The molecular formula is C15H18FN2O3Cl, and the molecular weight is 328.77 g/mol. The structural formula is:

Acoramidis HCl is a white to tan solid. The solubility of acoramidis is ≥ 12 micrograms/mL from pH 1.2 to 6.8 in aqueous media.

ATTRUBY is supplied as a white, film-coated, oval tablet, contains 356 mg acoramidis, printed with the BridgeBio company logo followed by “ACOR” in black ink on one side.

The inactive ingredients are croscarmellose sodium, magnesium stearate, microcrystalline cellulose, and silicon dioxide. The film coating and printing ink contain black iron oxide, glyceryl monocaprylocaprate, hypromellose, polyvinyl alcohol, propylene glycol, talc, titanium dioxide, and vinyl alcohol graft copolymer.

12 CLINICAL PHARMACOLOGY

12.1 Mechanism of Action

Acoramidis is a selective stabilizer of transthyretin (TTR). Acoramidis binds TTR at thyroxine binding sites and slows dissociation of the TTR tetramer into its constituent monomers, the rate-limiting step in amyloidogenesis.

12.2 Pharmacodynamics

TTR Stabilization

Changes in serum TTR level or in vitro TTR stabilization assays were utilized as pharmacodynamic markers of TTR stabilization. Increases in mean serum TTR levels were observed by Day 28 in ATTR-CM patients treated with ATTRUBY. Near-complete in vitro TTR stabilization was observed as early as Day 28 and through completion of a 30-month study of patients with ATTR-CM (wild-type and variant) treated with the recommended dosage [see Clinical Studies (14)].

Free thyroxine

ATTRUBY may decrease serum concentrations of free thyroxine without an accompanying change in thyroid stimulating hormone (TSH). A reduction in free thyroxine values has been observed with transthyretin stabilizers probably due to reduced thyroxine binding to or displacement from transthyretin (TTR).

NT-proBNP and Troponin I

In a clinical study of ATTRUBY in patients with ATTR-CM, at Month 30, the increase in N-terminal prohormone of brain natriuretic peptide [NT-proBNP] and troponin I was lower with ATTRUBY versus placebo. The increase in NT-proBNP at Month 30 for ATTRUBY was about half that of placebo [see Clinical Studies (14)].

Cardiac Electrophysiology

At approximately 1.2 times the steady state peak plasma concentrations (Cmax) at the recommended dose, ATTRUBY does not prolong the QTc interval to any clinically relevant extent.

12.3 Pharmacokinetics

The systemic exposures (Cmax and AUC) increase in a less than dose proportional manner following single and multiple doses of acoramidis. Over the dose range from 89 mg twice daily to 712 mg twice daily, AUC increases only 130%. Acoramidis steady state is achieved by 4 days with approximately 1.3-fold accumulation at the approved recommended dosage. At steady state, a dose of 712 mg twice daily results in a mean (SD) Cmax of 13700 (6090) ng/mL and AUC0-12h of 47200 (10300) ng.h/mL.

Absorption

The time to Cmax of acoramidis (Tmax) is approximately 1 hour following oral administration.

Effect of Food

No clinically significant differences in acoramidis pharmacokinetics were observed following administration of a high-fat meal (800-1000 total calories, ≥ 50% fat).

Distribution

The apparent steady-state volume of distribution for acoramidis is 654 liters. Acoramidis is 96% bound to human plasma proteins in vitro. Acoramidis primarily binds to TTR.

Elimination

The effective half-life of acoramidis is approximately 6 hours with a steady state apparent clearance of 16 L/hr.

Metabolism

Acoramidis is primarily metabolized by glucuronidation via UGT1A9, UGT1A1 and UGT2B7. Acoramidis-β-D-glucuronide (Acoramidis-AG) is the predominant metabolite of acoramidis (8% of total circulating drug related moieties).

Acoramidis-AG is approximately 1/3 as pharmacologically active compared with acoramidis, has a low potential for covalent binding, and does not contribute to pharmacological activity.

Excretion

After a single oral dose of radiolabeled acoramidis 712 mg to healthy adult subjects, approximately 32% of the dose radioactivity was recovered in feces (15% unchanged), and approximately 68% was recovered in urine (<10% unchanged).

Specific Populations

No clinically significant differences in the pharmacokinetics of acoramidis were observed based on age, race/ethnicity (including Japanese and non-Japanese), sex, or renal impairment. The effect of hepatic impairment (Child Pugh A, B, or C) on acoramidis pharmacokinetics is unknown.

Drug Interaction Studies

Clinical Studies

Following the administration of acoramidis (712 mg, BID) in a clinical study in healthy adult volunteers, there was not a clinically significant increase in exposure to the organic anion transporter-1 (OAT1) substrate (adefovir) and to OAT3 substrate (oseltamivir carboxylate).

Concomitant diuretic use in patients does not affect steady-state plasma acoramidis concentrations.

In Vitro Studies

Cytochrome P450 Enzymes:

Acoramidis is a time-dependent inhibitor of CYP2C9, but does not inhibit CYP1A2, CYP2B6, CYP2C8, CYP2C19, CYP2D6, or CYP3A4/5. Acoramidis does not induce CYP1A2, CYP2B6, or CYP3A4.

UDP-Glucuronosyl Transferase (UGT):

Acoramidis is a substrate of multiple UGT enzymes including UGT1A9, UGT1A1, and UGT2B7.

Transporter Systems:

Acoramidis is a substrate for OAT1 and breast cancer resistance protein (BCRP).

Acoramidis inhibits OAT1 and OAT3, but does not inhibit MATE1, OCT1, OCT2, OATP1B1, OATP1B3, MATE2-K, BCRP, P-gp, or BSEP.

13 NONCLINICAL TOXICOLOGY

13.1 Carcinogenesis, Mutagenesis, Impairment of Fertility

Carcinogenesis

There was no evidence of increased incidence of neoplasia in a 2-year carcinogenicity study in male rats dosed up to 50 mg/kg and in female rats dosed up to 350 mg/kg, which provided exposures approximately equivalent to and 11 times the AUC at the maximum recommended human dose (MRHD), respectively. There was no evidence of an increased incidence of neoplasia in transgenic (Tg.rasH2) mice following repeated daily administration for 26 weeks at daily doses up to 300 mg/kg.

Mutagenesis

There was no evidence of mutagenicity or clastogenicity for acoramidis in an Ames assay or in vivo rat micronucleus and alkaline comet assay.

Impairment of Fertility

In a male and female fertility study, rats were orally administered acoramidis at 0, 50, 350, and 1,000 mg/kg/day. Male rats were given acoramidis prior to and during cohabitation for a total of up to 52 days. Female rats were given acoramidis prior to and during cohabitation until implantation of the embryo (Gestational Day 7) for a total of up to 34 days. There were no effects on fertility, reproductive performance, or mating behavior in male or female rats at doses up to 1,000 mg/kg/day, approximately 38-times the AUC at the MRHD.

14 CLINICAL STUDIES

The efficacy of ATTRUBY was demonstrated in a multicenter, international, randomized, double-blind, placebo-controlled study in 611 adult patients with wild-type or variant (hereditary or de novo) ATTR-CM (NCT03860935).

Participants were randomized (2:1) to receive ATTRUBY 712 mg (n=409) or placebo (n=202) twice daily for 30 months. Treatment assignment was stratified by type of ATTR-CM [variant (ATTRv-CM) or wild-type (ATTRwt-CM)], NT-proBNP level, and estimated glomerular filtration rate (eGFR). The mean age of study participants was 77 years, 90.8% were male, 87.9% were White, 4.7% Black or African American, 2.1% Asian, 5.3% race other, 19% had a history of permanent pacemaker and 58% had a history of atrial fibrillation. No significant imbalance in baseline characteristics was observed between the two treatment groups.

Participants were permitted to initiate open-label tafamidis after 12 months in the study. A total of 107 participants received tafamidis: 61 (14.9%) in the ATTRUBY arm and 46 (22.8%) in the placebo arm. The median time to initiation of tafamidis for these 107 participants was 17 months.

The primary composite endpoint included all-cause mortality (ACM) and cumulative frequency of cardiovascular-related hospitalizations (CVH) over 30 months, analyzed hierarchically using the stratified Finkelstein-Schoenfeld (F-S) test. The F-S test demonstrated a statistically significant reduction (p=0.018) in ACM and cumulative frequency of CVH in the ATTRUBY arm versus the placebo arm. All-cause mortality was reported in 19% and 26% of participants in the ATTRUBY and placebo groups, respectively. The majority (79%) of the deaths were cardiovascular. CVH was reported in 27% and 43% of participants in the ATTRUBY and placebo groups, respectively. The mean number of CVH events was 0.3 vs 0.6 per year. The majority (59%) of CVH were heart failure hospitalizations reported in 13% and 26% of the participants in the ATTRUBY and placebo groups, respectively.

The treatment effect of ATTRUBY on functional capacity and health status was assessed by the 6MWD and the Kansas City Cardiomyopathy Questionnaire-Overall Summary score (KCCQ-OS) respectively. At month 30, the LS mean difference (95% CI) in change from baseline in 6MWD was 40 [21, 58] meters (p < 0.0001) and change from baseline in KCCQ-OS was 10 [6, 14] points (p < 0.0001) (Figure 1 and Figure 2).

Figure 1 - 6MWD Change from Baseline

Figure 2 - KCCQ-OS Score Change from Baseline

Abbreviations: 6MWD = Six-Minute Walk Distance; KCCQ-OS = Kansas City Cardiomyopathy Questionnaire Overall Summary Score; SE = standard error; LS = least squares.

The changes from baseline in 6MWT and KCCQ-OS were analyzed using the mixed model for repeated measures (MMRM) with treatment group, visit, genotype (ATTRv-CM vs ATTRwt-CM), NT-proBNP level (≤ 3000 vs > 3000 pg/mL), eGFR level (≥ 45 vs < 45 mL/min/1.73 m^2) and treatment group-by-visit interaction as factors, and baseline value as covariate.

A Cox regression analysis indicated a 35.5% decrease in the risk of the composite of ACM or first CV hospitalization (hazard ratio: 0.645 [95% CI: 0.500, 0.832]). A Kaplan-Meier plot of time to first event of ACM or CVH is shown in Figure 3.

Figure 3: Time to First All-cause Mortality or Cardiovascular-Related Hospitalization over Month 30, mITT Population

Figure 4 shows the treatment effects by prespecified subgroups.

Figure 4: Win-Ratio Analyses for Hierarchical Combination of All-Cause Mortality and Cardiovascular-Related Hospitalization by Overall and Subgroup, mITT Population

Abbreviations: ATTR-CM = transthyretin amyloid cardiomyopathy; ATTRv-CM = variant ATTR-CM; ATTRwt-CM = wild-type ATTR-CM; eGFR = estimated glomerular filtration rate; mITT = modified intent-to-treat; NAC = National Amyloidosis Centre; NT-proBNP = N-terminal prohormone of brain natriuretic peptide; NYHA = New York Heart Association
All-Cause Mortality includes heart transplant, CMAD and all-cause death. Cardiovascular-related hospitalizations include cardiovascular hospitalizations and urgent unplanned visits requiring treatment with intravenous diuretic for decompensated heart failure. Non-White includes American Indian or Alaska Native, Asian, Black or African American, Native Hawaiian or Other Pacific Islander, Other, multiple races and Not reported.
ATTR NAC Stage: ATTR Stage I, defined as NT-proBNP ≤ 3000 ng/L and eGFR ≥ 45 mL/min/1.73 m^2; Stage III, defined as NT-proBNP > 3000 ng/L and eGFR < 45 mL/min/1.73 m^2, the remainder categorized as Stage II.

16 HOW SUPPLIED/STORAGE AND HANDLING

ATTRUBY (acoramidis) tablets, 356 mg, are white, film-coated, oval tablets, printed with the BridgeBio company logo followed by “ACOR” in black ink on one side.

ATTRUBY tablets are supplied as a carton of 112 tablets: 4 blister cards (each containing 28 tablets)– (NDC 82228-712-28).

Store ATTRUBY at controlled room temperature 20°C to 25°C (68°F to 77°F); excursions permitted to 15°C to 30°C (59°F to 86°F) [see USP Controlled Room Temperature]. Store in original blister card until use to protect from moisture.

17 PATIENT COUNSELING INFORMATION

Advise the patient to read the FDA-approved patient labeling (Patient Information).

Pregnancy

Advise patients who are exposed to ATTRUBY during pregnancy to contact the BridgeBio reporting line at 1-844-550-2246. Advise patients to inform their healthcare provider of a known or suspected pregnancy [see Use in Specific Populations (8.1)].

For more information about ATTRUBY, go to www.ATTRUBY.com

Distributed by:
BridgeBio Pharma, Inc.
Palo Alto, CA 94304

PATIENT INFORMATION
ATTRUBYTM (ah-troo-be)
(acoramidis)
tablets

What is ATTRUBY?
ATTRUBY is a prescription medicine used to treat adults with a disease that affects the heart muscle called cardiomyopathy of wild-type or variant transthyretin-mediated amyloidosis (ATTR-CM), to reduce death and hospitalization related to heart problems.
It is not known if ATTRUBY is safe and effective in children.

Before taking ATTRUBY, tell your healthcare provider about all your medical conditions, including if you:

- are pregnant or plan to become pregnant. It is not known if ATTRUBY will harm your unborn baby. Tell your healthcare provider right away if you become pregnant or think you may be pregnant during treatment with ATTRUBY. You may also report your pregnancy by calling the BridgeBio reporting line at 1-844-550-2246.
- are breastfeeding or plan to breastfeed. It is not known if ATTRUBY passes into your breast milk. Talk to your healthcare provider about the best way to feed your baby during treatment with ATTRUBY.

Tell your healthcare provider about all the medicines you take, including prescription and over-the-counter medicines, vitamins, and herbal supplements.

How should I take ATTRUBY?

- Take ATTRUBY exactly as your healthcare provider tells you to.
- Take ATTRUBY tablets by mouth 2 times a day, with or without food.
- Swallow tablets whole. Do not cut, crush, or chew tablets.

What are the possible side effects of ATTRUBY?
The most common side effects of ATTRUBY were mild and include:

- stomach-area (abdominal) pain
- diarrhea

These are not all of the possible side effects of ATTRUBY.
Call your doctor for medical advice about side effects. You may report side effects to FDA at 1-800-FDA-1088.

How should I store ATTRUBY?

- Store ATTRUBY tablets at room temperature between 68°F to 77°F (20°C to 25°C).
- Store in original blister card until use to protect from moisture.

Keep ATTRUBY and all medicines out of the reach of children.

General information about the safe and effective use of ATTRUBY.
Medicines are sometimes prescribed for purposes other than those listed in a Patient Information leaflet. Do not use ATTRUBY for a condition for which it was not prescribed. Do not give ATTRUBY to other people, even if they have the same symptoms you have. It may harm them. You can ask your pharmacist or healthcare provider for information about ATTRUBY that is written for health professionals.

What are the ingredients in ATTRUBY?
Active ingredient: acoramidis
Inactive ingredients: croscarmellose sodium, magnesium stearate, microcrystalline cellulose, and silicon dioxide. The film coating and printing ink contain black iron oxide, glyceryl monocaprylocaprate, hypromellose, polyvinyl alcohol, propylene glycol, talc, titanium dioxide, and vinyl alcohol graft copolymer.

Distributed by: BridgeBio Pharma, Inc., Palo Alto, CA 94304

For more information about ATTRUBY, go to www.ATTRUBY.com or call 1-844-550-2246

This Patient Information has been approved by the U.S. Food and Drug Administration.

Issued: 11/2024

Principal Display Panel – 356 mg Carton Label

NDC 82228-712-28

Rx only

bridgebio

Attruby™

(acoramidis) tablets

356 mg per tablet

Take two 356 mg tablets two times a day
(712 mg dose two times a day)

Four 7-day blister cards
with 28 tablets per card
(112 tablets)